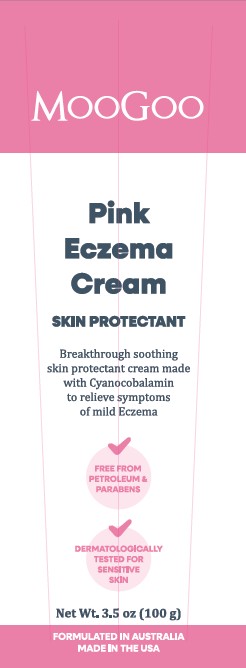 DRUG LABEL: Pink Eczema Cream
NDC: 87043-0012 | Form: CREAM
Manufacturer: MOOGOO SKIN CARE PTY LTD
Category: otc | Type: HUMAN OTC DRUG LABEL
Date: 20251104

ACTIVE INGREDIENTS: OATMEAL 0.5 g/100 g
INACTIVE INGREDIENTS: SIMMONDSIA CHINENSIS (JOJOBA) SEED OIL; MALVA SYLVESTRIS LEAF; COCOS NUCIFERA (COCONUT) OIL; NIGELLA SATIVA SEED OIL; WATER; PRUNUS AMYGDALUS DULCIS (SWEET ALMOND) OIL; P-ANISIC ACID; XANTHAN GUM; HOPS; PIROCTONE OLAMINE; CETEARYL ALCOHOL; ALLANTOIN; BISABOLOL; POLYSORBATE 60; .ALPHA.-TOCOPHEROL ACETATE, D-; CITRIC ACID; CYANOCOBALAMIN; ALOE BARBADENSIS LEAF; OLEA EUROPAEA (OLIVE) OIL UNSAPONIFIABLES; SQUALANE; GLYCERIN

PURPOSE

Skin Protectant

INDICATIONS AND USAGE

Breakthrough soothing skin protectant cream made with Cyanocobalamin to relieve symptoms of mild Eczema

Drug Facts

Active ingredient

Colloidal Oatmeal 0.05% w/w

Uses

Temporarily protects and helps relieve minor skin irritation and itching due to:

rashes

eczema

Warnings

For external use only

When using this product

Do not get into eyes

Stop use and ask a doctor if:

Conditions worsens

Symptoms last more than 7 days or clear up and occur again within a few days.

Keep out of reach of children.

If swallowed, get medical help or contact a Poison Control Center right away.

Directions

Apply as needed.

Other Information

Store below 86°F

Inactive Ingredients

Water, Prunus Amygdalus Dulcis (Sweet Almond) Oil, Cetearyl Alcohol, Cocos Nucifera (Coconut) Oil, Simmondsia Chinensis (Jojoba) Seed Oil, Nigella Sativa Seed Oil, Squalane, Polysorbate 60, Tocopheryl Acetate, Malva Sylvestris (Mallow) Extract, Piroctone Olamine, Allantoin, Glycerin, p-Anisic Acid, Olea Europaea (Olive) Oil, Citric Acid, Xanthan Gum, Bisabolol, Cyanocobalamin, Aloe Barbadensis Leaf Juice Powder, Humulus Lupulus (Hops) Extract.

Questions or comments?

Phone +844 753 4153

front-of-label text

<paragraph>MooGoo</paragraph>
<paragraph>Pink Eczema Cream</paragraph>
<paragraph>Skin Protectant</paragraph>
<paragraph>Breakthrough soothing skin protectant cream made with Cyanocobalamin to relieve symptoms of mild eczema</paragraph>
<paragraph>Net Wt. 4.2 oz (120 g)</paragraph>
<paragraph>Formulated in Australia Made in the USA</paragraph>